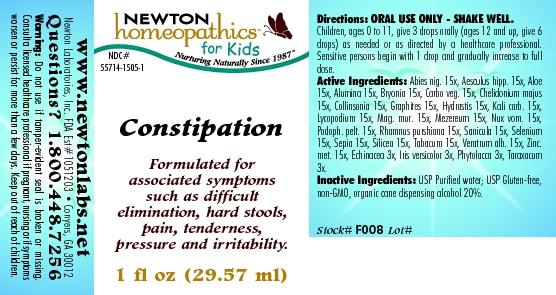 DRUG LABEL: Constipation 
NDC: 55714-1505 | Form: LIQUID
Manufacturer: Newton Laboratories, Inc.
Category: homeopathic | Type: HUMAN OTC DRUG LABEL
Date: 20110301

ACTIVE INGREDIENTS: Picea Mariana Resin 15 [hp_X]/1 mL; Horse Chestnut 15 [hp_X]/1 mL; Aloe 15 [hp_X]/1 mL; Aluminum Oxide 15 [hp_X]/1 mL; Bryonia Alba Root 15 [hp_X]/1 mL; Activated Charcoal 15 [hp_X]/1 mL; Chelidonium Majus 15 [hp_X]/1 mL; Collinsonia Canadensis Root 15 [hp_X]/1 mL; Graphite 15 [hp_X]/1 mL; Goldenseal 15 [hp_X]/1 mL; Potassium Carbonate 15 [hp_X]/1 mL; Lycopodium Clavatum Spore 15 [hp_X]/1 mL; Magnesium Chloride 15 [hp_X]/1 mL; Daphne Mezereum Bark 15 [hp_X]/1 mL; Strychnos Nux-vomica Seed 15 [hp_X]/1 mL; Podophyllum 15 [hp_X]/1 mL; Frangula Purshiana Bark 15 [hp_X]/1 mL; Sanicula Europaea Leaf 15 [hp_X]/1 mL; Selenium 15 [hp_X]/1 mL; Sepia Officinalis Juice 15 [hp_X]/1 mL; Silicon Dioxide 15 [hp_X]/1 mL; Tobacco Leaf 15 [hp_X]/1 mL; Veratrum Album Root 15 [hp_X]/1 mL; Zinc 15 [hp_X]/1 mL; Echinacea, Unspecified 3 [hp_X]/1 mL; Iris Versicolor Root 3 [hp_X]/1 mL; Phytolacca Americana Root 3 [hp_X]/1 mL; Taraxacum Officinale 3 [hp_X]/1 mL
INACTIVE INGREDIENTS: Alcohol

Constipation

INDICATIONS & USAGE SECTION

Constipation Formulated for associated symptoms such as difficult elimination, hard stools, pain, tenderness, pressure and irritability.

DOSAGE & ADMINISTRATION SECTION

Directions: ORAL USE ONLY - SHAKE WELL. Children, ages 0 to 11, give 3 drops orally (ages 12 and up, give 6 drops) as needed or as directed by a healthcare professional. Sensitive persons begin with 1 drop and gradually increase to full dose.

OTC - ACTIVE INGREDIENT SECTION

Abies nig. 15x, Aesculus hipp. 15x, Aloe 15x, Alumina 15x, Bryonia 15x, Carbo veg. 15x, Chelidonium majus 15x, Collinsonia 15x, Graphites 15x, Hydrastis 15x, Kali carb. 15x, Lycopodium 15x, Mag. mur. 15x, Mezereum 15x, Nux vom. 15x, Podoph. pelt. 15x, Rhamnus purshiana 15x, Sanicula 15x, Selenium 15x, Sepia 15x, Silicea 15x, Tabacum 15x, Veratrum alb. 15x, Zinc.met. 15x, Echinacea 3x, Iris versicolor 3x, Phytolacca 3x, Taraxacum 3x.

OTC - PURPOSE SECTION

Formulated for associated symptoms such as difficult elimination, hard stools, pain, tenderness, pressure and irritability.

INACTIVE INGREDIENT SECTION

Inactive Ingredients: USP Purified Water; USP Gluten-free, non-GMO, organic cane dispensing alcohol 20%.

QUESTIONS SECTION

www.newtonlabs.net Newton Laboratories, Inc. FDA Est # 1051203 - Conyers, GA 30012
Questions? 1.800.448.7256

WARNINGS SECTION

Warning: Do not use if tamper - evident seal is broken or missing. Consult a licensed healthcare professional if pregnant, nursing or if symptoms worsen or persist for more than a few days. Keep out of reach of children.

OTC - PREGNANCY OR BREAST FEEDING SECTION

Consult a licensed healthcare professional if pregnant, nursing or if symptoms worsen or persist for more than a few days.

OTC - KEEP OUT OF REACH OF CHILDREN SECTION

Keep out of reach of children.